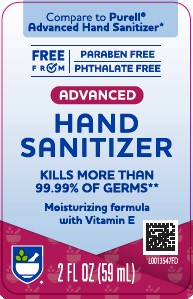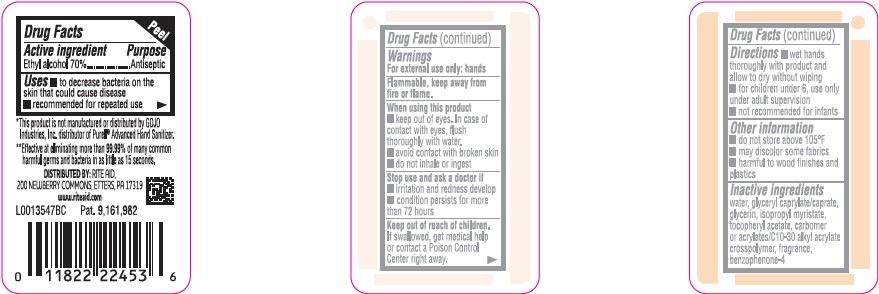 DRUG LABEL: Advanced Hand Sanitizer
NDC: 11822-3700 | Form: GEL
Manufacturer: Rite Aid Corporation
Category: otc | Type: HUMAN OTC DRUG LABEL
Date: 20260130

ACTIVE INGREDIENTS: ALCOHOL 70 mL/100 mL
INACTIVE INGREDIENTS: GLYCERYL CAPRYLATE/CAPRATE; GLYCERIN; WATER; ISOPROPYL MYRISTATE; .ALPHA.-TOCOPHEROL ACETATE; CARBOMER HOMOPOLYMER, UNSPECIFIED TYPE; CARBOMER COPOLYMER TYPE B (ALLYL PENTAERYTHRITOL CROSSLINKED); SULISOBENZONE

Daylogic 370.001/370AB-AE rev 1
Advanced Hand Sanitizer

Active Ingredient

Ethyl alcohol 70%

Purpose

Antiseptic

Uses

- to decrease bacteria on the skin that could cause disease
- recommended for repeated use

Warnings

For external use only: hands

Flammable, keep away from fire or flame.

When using this product

- keep out of eyes. In case of contact with eyes, flush thoroughly with water.
- avoid contact with broken skin
- do not inhale or ingest

Stop use and ask a doctor if

- irritation and redness develop
- condition persists for more than 72 hours

Keep out of reach of children.

If swallowed, get medical help or contact a Poison Control Center right away.

Directions

- wet hands thoroughly with product and allow to dry without wiping
- for children under 6, use only under adult supervision
- not recommended for infants

Other information

- do not store above 105⁰F
- may discolor some fabrics
- harmful to wood finishes and plastics

Inactive ingredients

water, glyceryl caprylate/caprate, glycerin, isopropyl myristate, tocopheryl acetate, carbomer or acrylates/C10-30 alkyl acrylate crosspolymer, fragrance, benzophenone-4

Disclaimer

*This product is not manufactured or distributed by GoJo Industries, Inc., distributor of Purell® Advanced Hand Sanitizer.

Claim

**Effective at eliminating more than 99.99% of many common harmful germs and bacteria in as little as 15 seconds.

ADVERSE REACTION

DISTRIBUTED BY: RITE AID

200 NEWBERRY COMMONS, ETTERS, PA 17319

www.riteaid.com

Pat. 9,161,982

principal display panel

Compare to Purell®Advanced Hand Sanitizer*

FREE FROM:

- PARABEN FREE
- PHTHALATE FREE

ADVANCED

HAND SANITIZER

KILLS MORE THAN 99.99% OF GERMS**

Moisturizing formula with Vitamin E

2 FL OZ (59 mL)